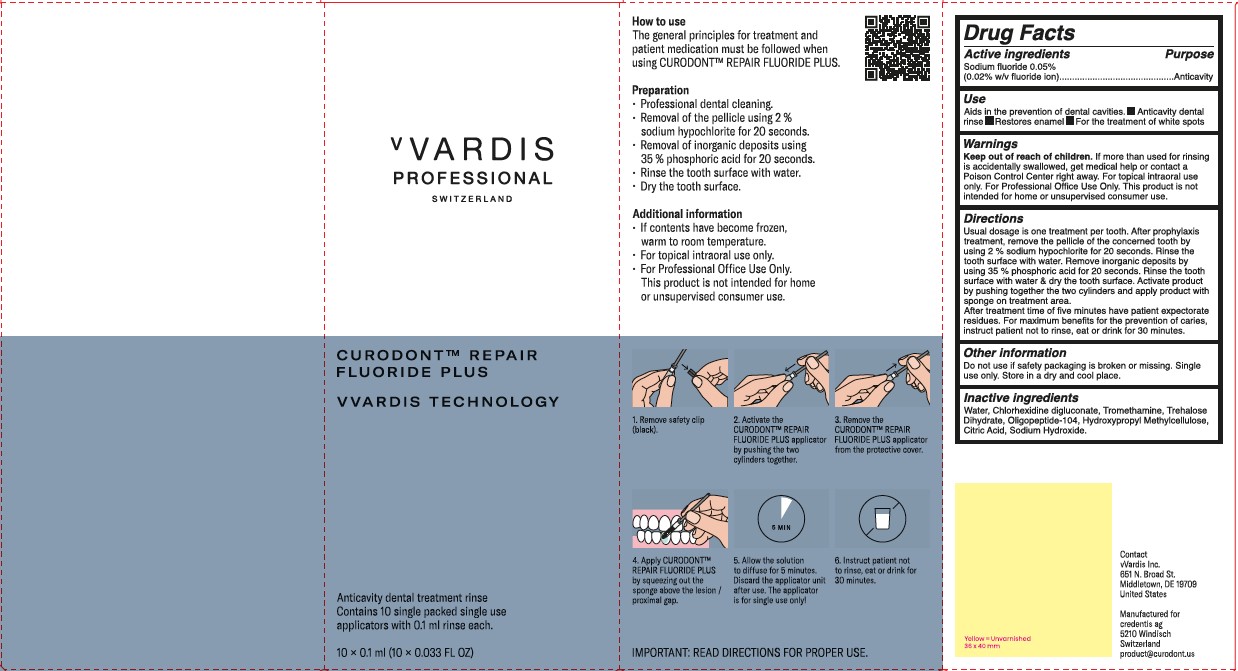 DRUG LABEL: CURODONT REPAIR FLUORIDE PLUS
NDC: 72247-109 | Form: SPONGE
Manufacturer: CREDENTIS AG
Category: otc | Type: HUMAN OTC DRUG LABEL
Date: 20241201

ACTIVE INGREDIENTS: SODIUM FLUORIDE 0.02 g/100 mL
INACTIVE INGREDIENTS: ANHYDROUS CITRIC ACID; SODIUM HYDROXIDE; WATER; CHLORHEXIDINE GLUCONATE; TROMETHAMINE; TREHALOSE DIHYDRATE; OLIGOPEPTIDE 104; HYPROMELLOSE, UNSPECIFIED

CREDENTIS (Gen 2) - vVardis Professional - CURODONT REPAIR FLUORIDE PLUS (72247-109)

ACTIVE INGREDIENTS

SODIUM FLUORIDE 0.05%

(0.02% W/V FLUORIDE ION)

PURPOSE

ANTICAVITY

USES

AIDS IN THE PREVENTION OF DENTAL CAVITIES

- ANTICAVITY DENTAL RINSE
- RESTORES ENAMEL
- FOR THE TREATMENT OF WHITE SPOTS

WARNINGS

FOR TOPICAL INTRAORAL USE ONLY. FOR PROFESSIONAL OFFICE USE ONLY. THIS PRODUCT IS NOT INTENDED FOR HOME OR UNSUPERVISED CONSUMER USE.

KEEP OUT OF REACH OF CHILDREN. IF MORE THAN USED FOR RINSING IS ACCIDENTALLY SWALLOWED, GET MEDICAL HELP OR CONTACT A POISON CONTROL CENTER RIGHT AWAY.

DIRECTIONS

Usual dosage is one treatment per tooth. After prophylaxis treatment, remove the pellicle of the concerned tooth by using 2% sodium hypochlorite for 10 seconds. Rinse the tooth surface with water. Remove inorganic deposits by pushing together the two cylinders and apply product with sponge on treatment area.

After treatment time of five minutes have patient expectorate residues. For maximum benefits for the prevention of caries, instruct patient not to rinse, eat or drink for 30 minutes.

OTHER INFORMATION

DO NOT USE IF SAFETY PACHAGING IS BROKEN OR MISSING.

SINGLE USE ONLY.

STORE IN A DRY AND COOL PLACE.

INACTIVE INGREDIENTS

WATER, CHLORHEXIDINE DIGLUCONATE, TROMETHAMINE, TREHALOSE DIHYDRATE, OLIGOPEPTIDE-104, HYDROXYPROPYL METHYLCELLULOSE, CITRIC ACID, SODIUM HYDROXIDE.